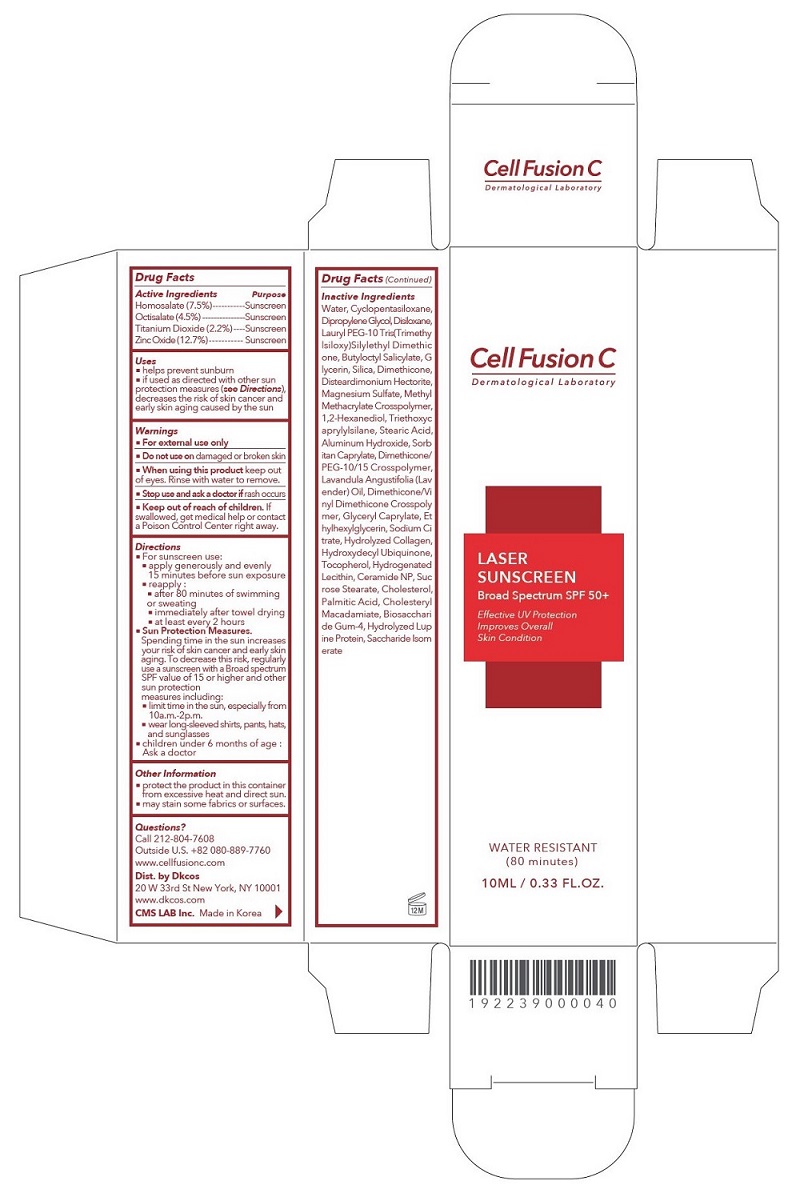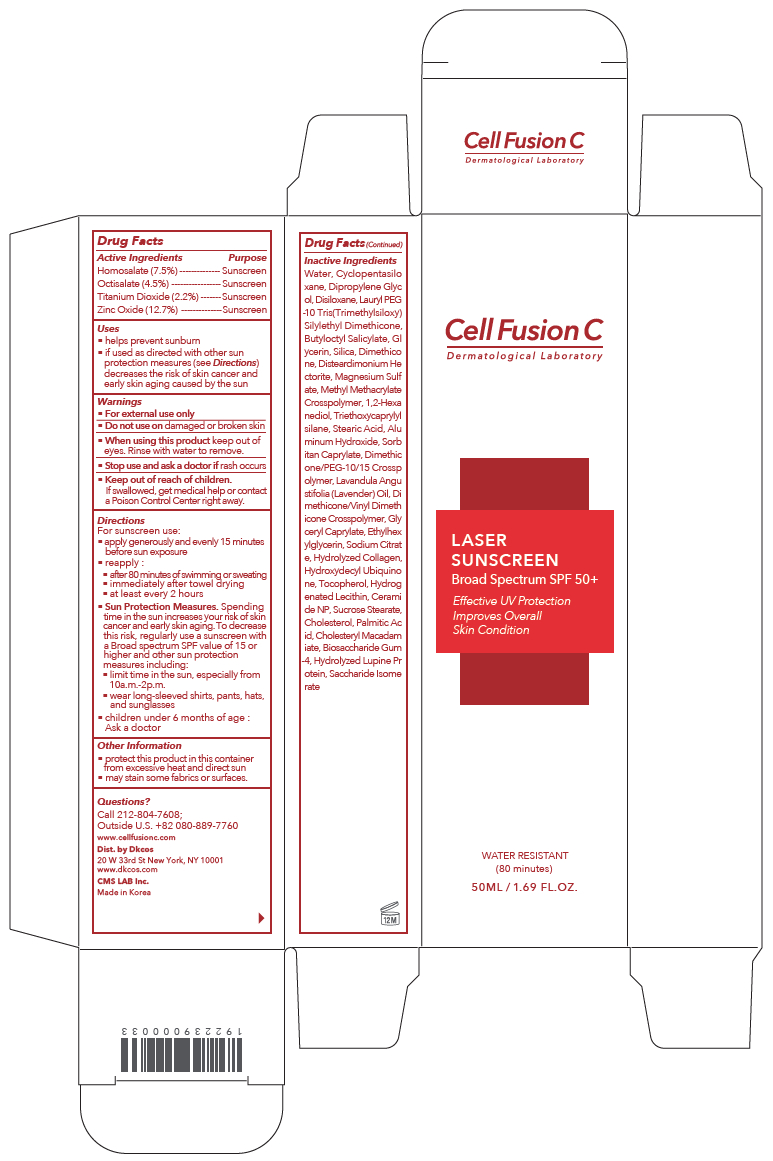 DRUG LABEL: Cell Fusion C Laser Sunscreen Broad Spectrum SPF 50
NDC: 52554-9052 | Form: CREAM
Manufacturer: CMS LAB Inc.
Category: otc | Type: HUMAN OTC DRUG LABEL
Date: 20241201

ACTIVE INGREDIENTS: HOMOSALATE 7.5 g/50 mL; ZINC OXIDE 12.7 g/50 mL; OCTISALATE 4.5 g/50 mL; TITANIUM DIOXIDE 2.2 g/50 mL
INACTIVE INGREDIENTS: WATER

Cell Fusion C Laser Sunscreen Broad Spectrum SPF 50+

Drug Facts

ACTIVE INGREDIENTS

Homosalate 7.5%
Octisalate 4.5%
Titanium Dioxide 2.2%
Zinc Oxide 12.7%

PURPOSE

Sunscreen

USES

- helps prevent sunburn
- if used as directed with other sun protection measures (see Directions), decreases the risk of skin cancer and early skin aging caused by the sun

WARNINGS

For external use only

- Do not use ondamaged or broken skin

WHEN USING

- When using this productkeep out of the eyes. Rinse with water to remove.

- Stop use and ask a doctorif rash occurs

- Keep out of reach of children.If swallowed, get medical help or contact a Poison Control Center right away.

DIRECTIONS For sunscreen use:

- apply generously and evenly 15 minutes before sun exposure
- reapply:
- after 80 minutes of swimming or sweating
- immediately after towel drying
- at least every 2 hours
- Sun Protection Measures. Spending time in the sun increases your risk of skin cancer and early skin aging. To decrease this risk, regularly use a sunscreen with a Broad Spectrum SPF value of 15 or higher and other sun protection measures including:

- limit time in the sun, especially from 10 a.m.-2 p.m.
- wear long-sleeved shirts, pants, hats, and sunglasses
- children under 6 months of age: Ask a doctor

OTHER INFORMATION

- protect the product in this container from excessive heat and direct sun
- may stain some fabrics or surfaces.

INACTIVE INGREDIENTS

WATER, CYCLOPENTASILOXANE, DIPROPYLENE GLYCOL, DISILOXANE, LAURYL PEG-10 TRIS(TRIMETHYLSILOXY) SILYLETHYL DIMETHICONE, GLYCERIN, BUTYLOCTYL SALICYLATE, SILICA, DIMETHICONE, DISTEARDIMONIUM HECTORITE, MAGNESIUM SULFATE, METHYL METHACRYLATE CROSSPOLYMER, 1,2-HEXANEDIOL, TRIETHOXYCAPRYLYLSILANE, STEARIC ACID, ALUMINUM HYDROXIDE, SORBITAN CAPRYLATE, DIMETHICONE/PEG-10/15 CROSSPOLYMER, LAVANDULA ANGUSTIFOLIA (LAVENDER) OIL, DIMETHICONE/VINYL DIMETHICONE CROSSPOLYMER, GLYCERYL CAPRYLATE, ETHYLHEXYLGLYCERIN, SODIUM CITRATE, HYDROXYDECYL UBIQUINONE, HYDROLYZED COLLAGEN, TOCOPHEROL, HYDROGENATED LECITHIN, CERAMIDE NP, SUCROSE STEARATE, CHOLESTEROL, CHOLESTERYL MACADAMIATE, PALMITIC ACID, BIOSACCHARIDE GUM-4, SACCHARIDE ISOMERATE, HYDROLYZED LUPINE PROTEIN

QUESTIONS?

Call 212-804-7608
Outside U.S. +82 080-889-7760
www.cellfusionc.com

Dist. by Dkcos
20 W 33rd St New York, NY 10001
www.dkcos.com

CMS LAB Inc.

Made in Korea

PRINCIPAL DISPLAY PANEL: 50ML / 1.69 FL.OZ. Carton

Cell Fusion C

Dermatological Laboratory

LASER
SUNSCREEN
Broad Spectrum SPF 50+

Effective UV Protection
Improve Overall
Skin Condition

WATER RESISTANT
(80 minutes)

50ML / 1.69 FL.OZ.

10ML / 0.33 FL.OZ.